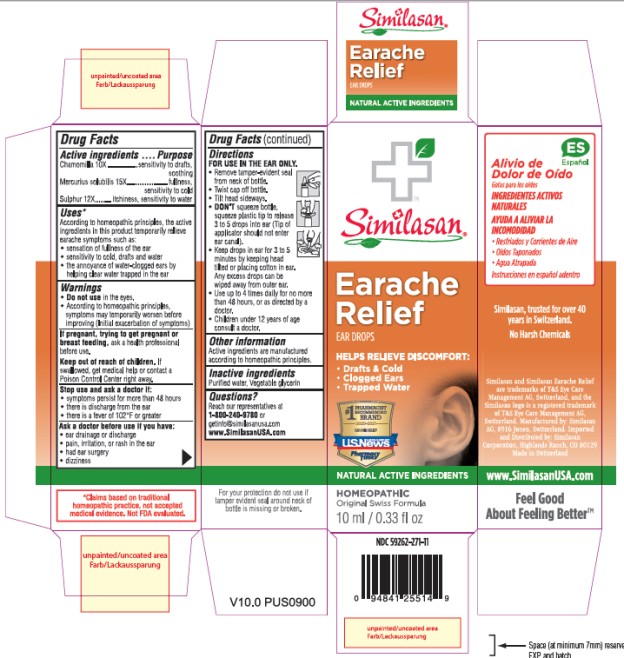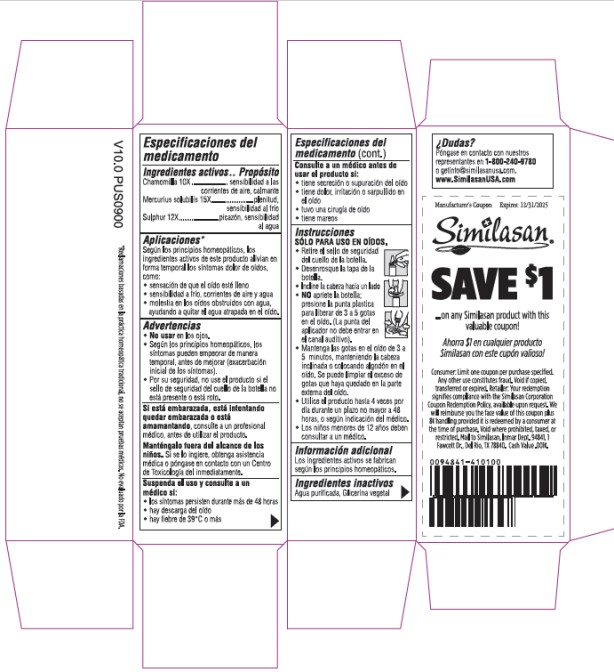 DRUG LABEL: Similasan Earache Relief
NDC: 59262-271 | Form: SOLUTION/ DROPS
Manufacturer: Similasan Corporation
Category: homeopathic | Type: HUMAN OTC DRUG LABEL
Date: 20250228

ACTIVE INGREDIENTS: MERCURIUS SOLUBILIS 15 [hp_X]/10 mL; CHAMOMILE 10 [hp_X]/10 mL; SULFUR 12 [hp_X]/10 mL
INACTIVE INGREDIENTS: WATER; GLYCERIN

Similasan Earache Relief

Drug Facts

Active ingredients

Chamomilla 10X

Purpose

sensitivity to drafts, soothing

Active ingredients

Mercurius solubilis 15X

Purpose

fullness, sensitivity to cold

Active ingredients

Sulphur 12X

Purpose

itchiness, sensitivity to water

Uses*

According to homeopathic principles, the active ingredients in this product temporarily relieve earache symptoms such as:

• sensation of fullness of the ear

• sensitivity to cold, drafts, and water

• the annoyance of water-clogged ears by helping clear water trapped in the ear

Warnings

Do not use

• in the eyes.

• According to homeopathic principles, symptoms may temporarily worsen before improving (Initial exacerbation of symptoms)

Keep out of reach of children.

If swallowed, get medical help or contact a Poison Control Center right away.

Stop use and ask a doctor if:

• symptoms persist for more than 48 hours

• there is discharge from the ear

• there is a fever of 102°F or greater

Ask a doctor before use if you have:

• ear drainage or discharge

• pain, irritation, or rash in the ear

• had ear surgery

• dizziness

Directions

FOR USE IN THE EAR ONLY.

• Remove tamper-evident seal from neck of bottle.

• Twist cap off bottle.

• Tilt head sideways.

• DON'T squeeze bottle, squeeze plastic tip to release 3 to 5 drops into ear (Tip of applicator should not enter ear canal).

• Keep drops in ear for 3 to 5 minutes by keeping head tilted or placing cotton in ear. Any excess drops can be wiped away from outer ear.

• Use up to 4 times daily for no more than 48 hours, or as directed by a doctor.

• Children under 12 years of age consult a doctor.

Other information

Active ingredients are manufactured according to homeopathic principles.

Inactive ingredient

Purified water, Vegetable glycerin

Questions?

Reach our representatives at 1-800-240-9780 or getinfo@similasanusa.com

www.SimilasanUSA.com

PRINCIPAL DISPLAY PANEL

NDC 59262-271-11
Similasan
Earache Relief
Ear Drops
10 ml/ 0.33 fl oz